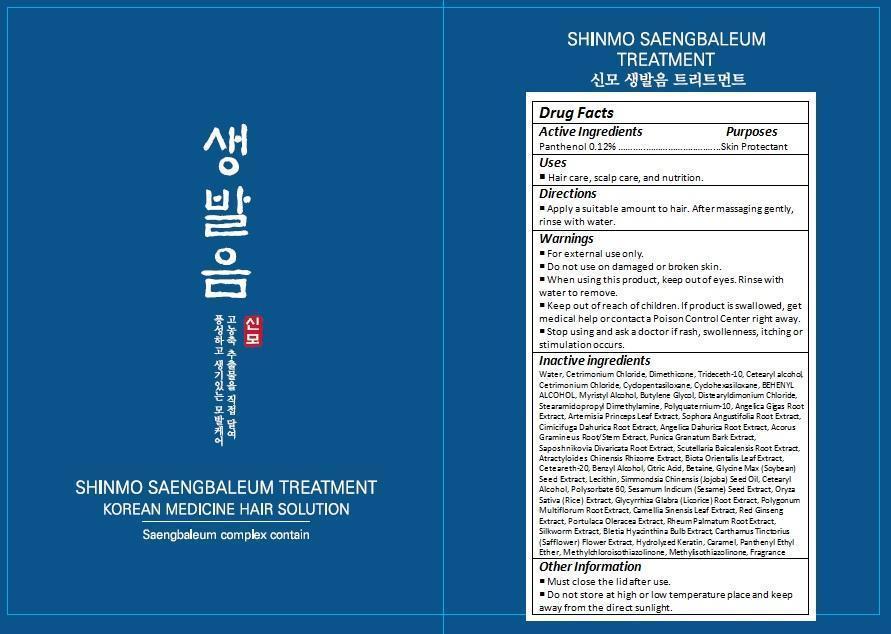 DRUG LABEL: SHINMO SAENGBALEUM TREATMENT
NDC: 69978-002 | Form: GEL
Manufacturer: ATEC&CO INC.
Category: otc | Type: HUMAN OTC DRUG LABEL
Date: 20150720

ACTIVE INGREDIENTS: PANTHENOL 0.95 g/958.50 g
INACTIVE INGREDIENTS: WATER; CETRIMONIUM CHLORIDE; TRIDECETH-10; CETOSTEARYL ALCOHOL; CYCLOMETHICONE 5; CYCLOMETHICONE 6; DOCOSANOL; MYRISTYL ALCOHOL; BUTYLENE GLYCOL; DISTEARYLDIMONIUM CHLORIDE; STEARAMIDOPROPYL DIMETHYLAMINE; POLYQUATERNIUM-10 (400 MPA.S AT 2%); ANGELICA GIGAS ROOT; ARTEMISIA PRINCEPS LEAF; SOPHORA FLAVESCENS ROOT; ACTAEA DAHURICA ROOT; ANGELICA DAHURICA ROOT; ACORUS GRAMINEUS ROOT; PUNICA GRANATUM ROOT BARK; SAPOSHNIKOVIA DIVARICATA ROOT; SCUTELLARIA BAICALENSIS ROOT; ATRACTYLODES LANCEA ROOT; PLATYCLADUS ORIENTALIS LEAF; POLYOXYL 20 CETOSTEARYL ETHER; BENZYL ALCOHOL; CITRIC ACID MONOHYDRATE; BETAINE; SOYBEAN; EGG PHOSPHOLIPIDS; JOJOBA OIL; POLYSORBATE 60; SESAME SEED; RICE GERM; GLYCYRRHIZA GLABRA; FALLOPIA MULTIFLORA ROOT; GREEN TEA LEAF; ASIAN GINSENG; PURSLANE; RHEUM PALMATUM ROOT; BLETILLA STRIATA BULB; SAFFLOWER; CARAMEL; PANTHENYL ETHYL ETHER; METHYLCHLOROISOTHIAZOLINONE; METHYLISOTHIAZOLINONE

Drug Facts

ACTIVE INGREDIENT

PANTHENOL 0.12%

PURPOSE

Cleansing

INDICATIONS AND USAGE

Strengthen hair roots and scalp. Keeps the hair rich and
Healthy.

DOSAGE AND ADMINISTRATION

Apply a suitable amount to hair. After massaging gently, rinse with water.

WARNINGS

For external use only.

Do not use on damaged or broken skin.

When using this product, keep out of eyes. Rinse with water to remove.

Stop using and ask a doctor if rash, swollenness, itching or stimulation occurs.

KEEP OUT OF REACH OF CHILDREN

Keep out of reach of the children. If product is swallowed, get medical help or contact a poison control center right away.

INACTIVE INGREDIENT

Water, Cetrimonium Chloride, Dimethicone, Trideceth-10, Cetearyl alcohol, Cetrimonium Chloride, Cyclopentasiloxane, Cyclohexasiloxane, BEHENYL ALCOHOL, Myristyl Alcohol, Butylene Glycol, Distearyldimonium Chloride, Stearamidopropyl Dimethylamine, Polyquaternium-10, Angelica Gigas Root Extract, Artemisia Princeps Leaf Extract, Sophora Angustifolia Root Extract, Cimicifuga Dahurica Root Extract, Angelica Dahurica Root Extract, Acorus Gramineus Root/Stem Extract, Punica Granatum Bark Extract, Saposhnikovia Divaricata Root Extract, Scutellaria Baicalensis Root Extract, Atractyloides Chinensis Rhizome Extract, Biota Orientalis Leaf Extract, Ceteareth-20, Benzyl Alcohol, Citric Acid, Betaine, Glycine Max (Soybean) Seed Extract, Lecithin, Simmondsia Chinensis (Jojoba) Seed Oil, Cetearyl Alcohol, Polysorbate 60, Sesamum Indicum (Sesame) Seed Extract, Oryza Sativa (Rice) Extract, Glycyrrhiza Glabra (Licorice) Root Extract, Polygonum Multiflorum Root Extract, Camellia Sinensis Leaf Extract, Red Ginseng Extract, Portulaca Oleracea Extract, Rheum Palmatum Root Extract, Silkworm Extract, Bletia Hyacinthina Bulb Extract, Carthamus Tinctorius (Safflower) Flower Extract, Hydrolyzed Keratin, Caramel, Panthenyl Ethyl Ether, Methylchloroisothiazolinone, Methylisothiazolinone, Fragrance